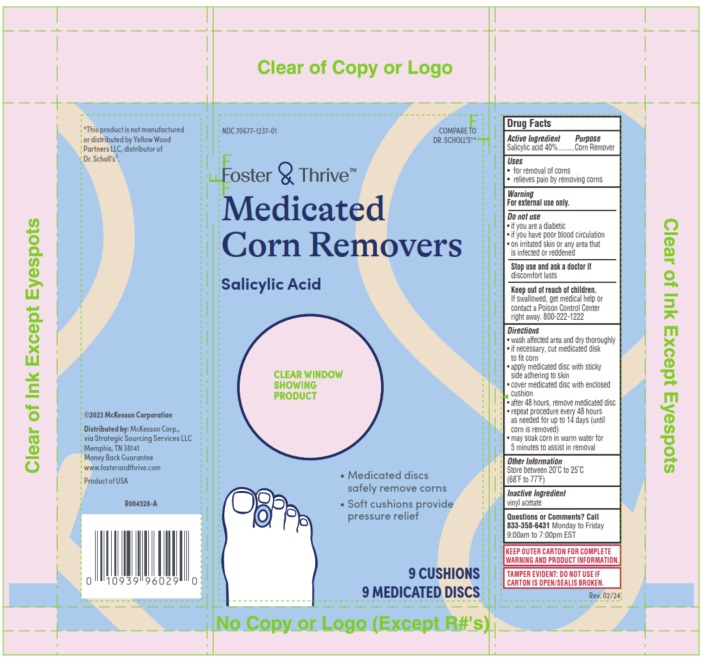 DRUG LABEL: Foster and Thrive Medicated Corn Removers
NDC: 70677-1237 | Form: PLASTER
Manufacturer: Strategic Sourcing Services LLC
Category: otc | Type: HUMAN OTC DRUG LABEL
Date: 20251205

ACTIVE INGREDIENTS: SALICYLIC ACID 40 mg/100 mg
INACTIVE INGREDIENTS: POLYVINYL ALCOHOL, UNSPECIFIED; ACRYLIC ACID/ETHYLENE COPOLYMER (600 MPA.S)

Foster and Thrive Medicated Corn Remover

Active Ingredient

Salicylic Acid 40%

Purpose

Corn Remover

Uses

- for removal of corns
- relieves pain by removing corns

Warning

For external use only

Do Not Use

- if you are a diabetic
- if you have poor blood circulation
- on irritated skin or area that is infected or reddened

Stop use and ask a doctor

if disomfort lasts

Keep out of reach of children

If swallowed get medical help or contact a Poison Control Center right away. 800-222-1222

Directions

- wash affected area, dry thoroughly
- If necessary, cut medicated disk to fit corn
- apply medicated disk with sitcky side adhereing to skin
- cover medicated disk with enclosed cushion
- after 48 hours, remove medicated disk
- repeat procedure every 48 hours as needed for up to 14 days (until corn is removed)
- may soak corn in warm water for 5 minutes to assist in removal

Other Information

Store between 20oC to 25oC (68oF to 77oF)

Inactive Ingredient

vinyl acetate